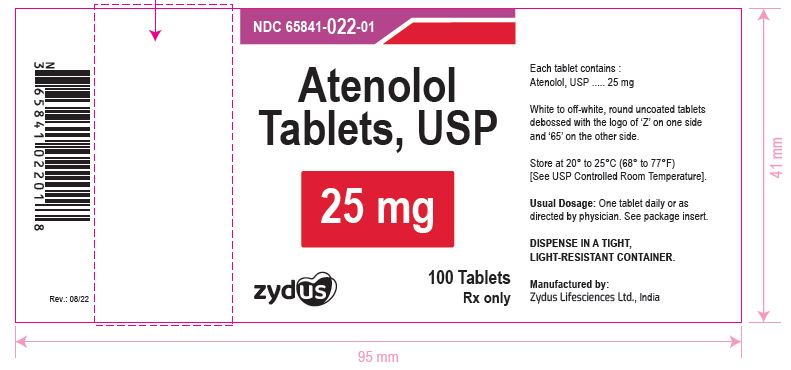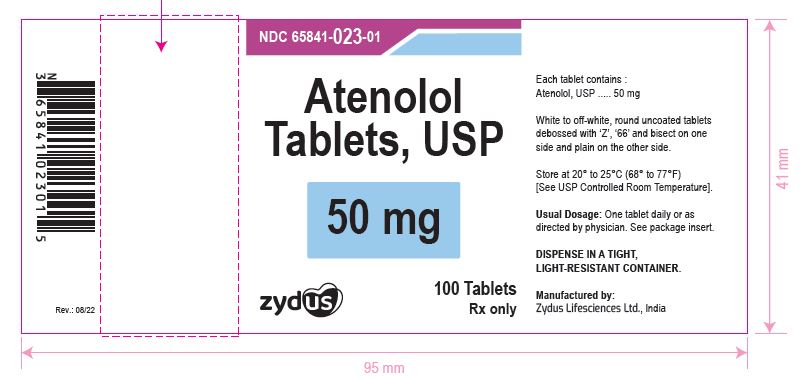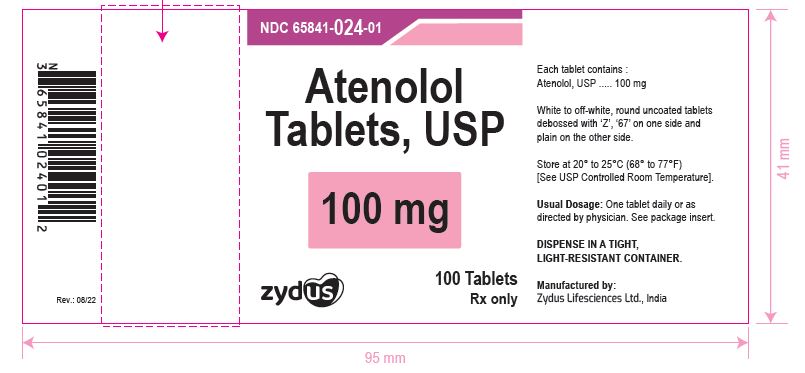 DRUG LABEL: Atenolol
NDC: 65841-022 | Form: TABLET
Manufacturer: Zydus Lifesciences Limited
Category: prescription | Type: HUMAN PRESCRIPTION DRUG LABEL
Date: 20241125

ACTIVE INGREDIENTS: ATENOLOL 25 mg/1 1
INACTIVE INGREDIENTS: ANHYDROUS CITRIC ACID; CROSCARMELLOSE SODIUM; MAGNESIUM STEARATE; SILICON DIOXIDE; POVIDONE; CELLULOSE, MICROCRYSTALLINE

Atenolol Tablets, USP

PACKAGE LABEL.PRINCIPAL DISPLAY PANEL

NDC 65841-022-01 in bottles of 100 tablets

Atenolol Tablets USP, 25 mg

Rx only

100 Tablets

NDC 65841-023-01 in bottles of 100 tablets

Atenolol Tablets USP, 50 mg

Rx only

100 Tablets

NDC 65841-024-01 in bottles of 100 tablets

Atenolol Tablets USP, 100 mg

Rx only

100 Tablets